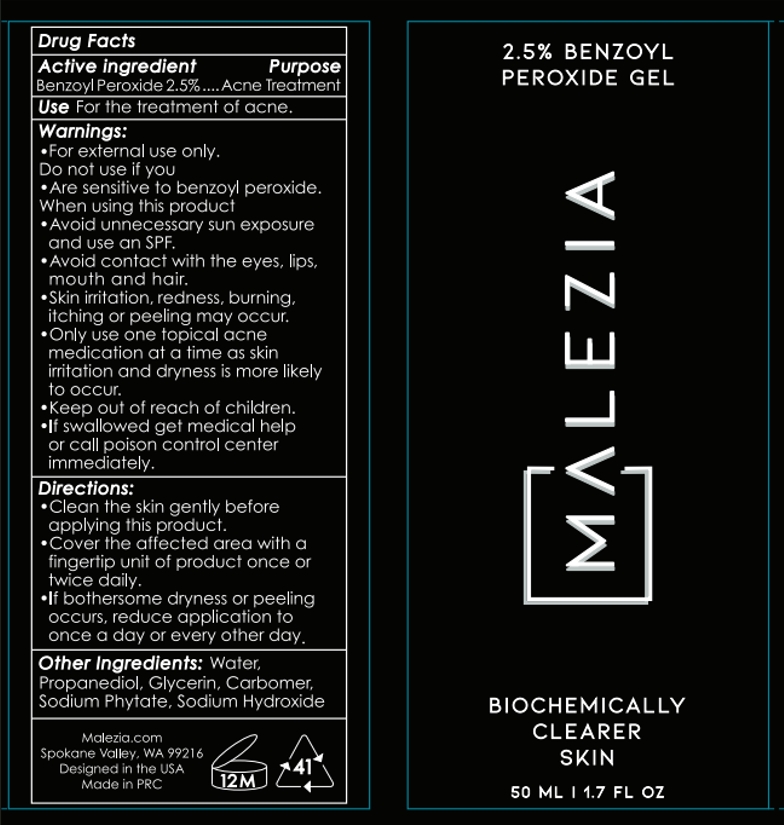 DRUG LABEL: Benzoyl Peroxide
NDC: 84339-001 | Form: GEL
Manufacturer: Enrich Enterprises Xiamen Limited
Category: otc | Type: HUMAN OTC DRUG LABEL
Date: 20240520

ACTIVE INGREDIENTS: BENZOYL PEROXIDE 2.5 mg/100 mL
INACTIVE INGREDIENTS: CARBOMER 980; SODIUM HYDROXIDE; PROPANEDIOL; PHYTATE SODIUM; WATER; GLYCERIN

84339-001

ACTIVE INGREDIENT

Benzoyl Peroxide 2.5%

PURPOSE

Acne Treatment

INDICATIONS AND USAGE

Use For the treatment of acne.

WARNINGS

- For external use only.

Do not use if you

- Are sensitive to benzoyl peroxide.

When using this product

- Avoid unnecessary sun exposure and use an SPF.

-Avoid contact with the eyes, lips, mouth and hair.

- Skin irritation, redness, burning, itching or peeling may occur.

- Only use one topical acne medication at a time as skin irritation and dryness is more likely to occur.

- Keep out of reach of children.

-If swallowed get medical help or call poison control center immediately.

STOP USE

- If swallowed get medical help or call poison control center immediately.

- Keep out of reach of children.

DOSAGE AND ADMINISTRATION

- Clean the skin gently before applying this product.

- Cover the affected area with a fingertip unit of product once or twice daily.

- If bothersome dryness or peeling occurs, reduce application to once a day or every other day.

INACTIVE INGREDIENT

Other Ingredients: Water, Propanediol, Glycerin, Carbomer, Sodium Phytate, Sodium Hydroxide